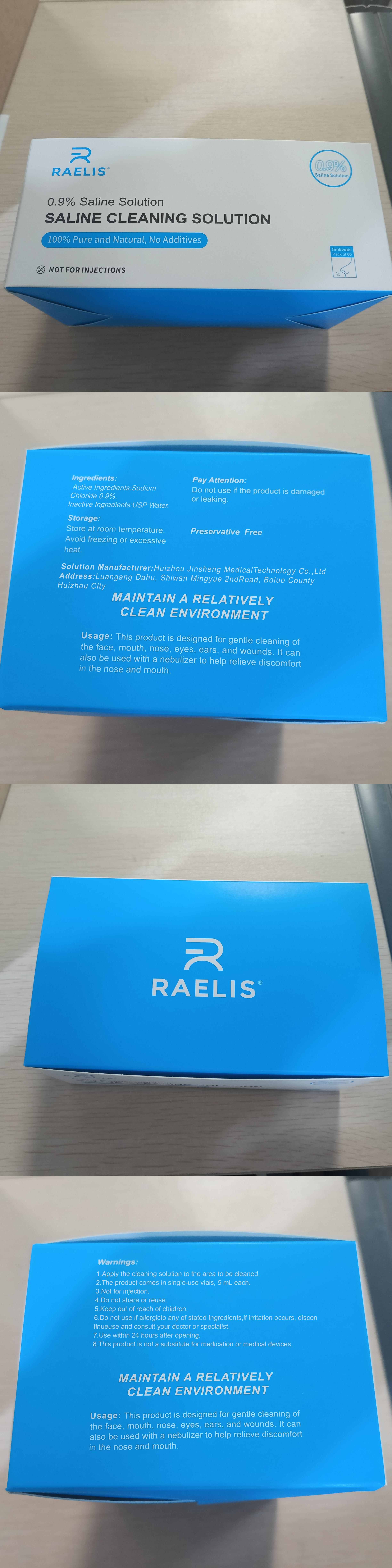 DRUG LABEL: 0.9%saline
NDC: 87311-103 | Form: SOLUTION
Manufacturer: Huizhou Jinsheng Medical Technology Co., Ltd
Category: otc | Type: HUMAN OTC DRUG LABEL
Date: 20260203

ACTIVE INGREDIENTS: SODIUM CHLORIDE 9 mg/1 mL
INACTIVE INGREDIENTS: WATER

0.9% saline

PURPOSE

Cleaning solution

Keep out of reach of children

INDICATIONS AND USAGE

Usage: This product is designed for gentle cleaning of the face, mouth, nose, eyes, ears, and wounds. It can also be used with a nebulizer to help relieve discomfort in the nose and mouth.

Warnings:
1.Apply the cleaning solution to the area to be cleaned.
2.The product comes in single-use vials, 5 mL each.
3.Not for injection.
4.Do not share or reuse.
5.Keep out of reach of children.
6.Do not use if allergic to any of stated Ingredients, if irritation occurs, discontinue use and consult your doctor or specialist.
7.Use within 24 hours after opening.

8.This product is not a substitute for medication or medical devices.

Single use dosage vials 5ml each

Active ingredient: Sodium Chloride 0.9%

Inactive ingredient: USP Water

OTHER SAFETY INFORMATION

Pay Attention: Do not use if the product is damaged or leaking.

QUESTIONS

Manufacturer:

Huizhou Jinsheng Medical Technology Co., Ltd

Luangang Dahu, Shiwan Mingyue 2nd Road, Boluo County, Huizhou, Guangdong, China, 516000

STORAGE AND HANDLING

Storage:Store at room temperature.Avoid freezing or excessive heat.

See Label